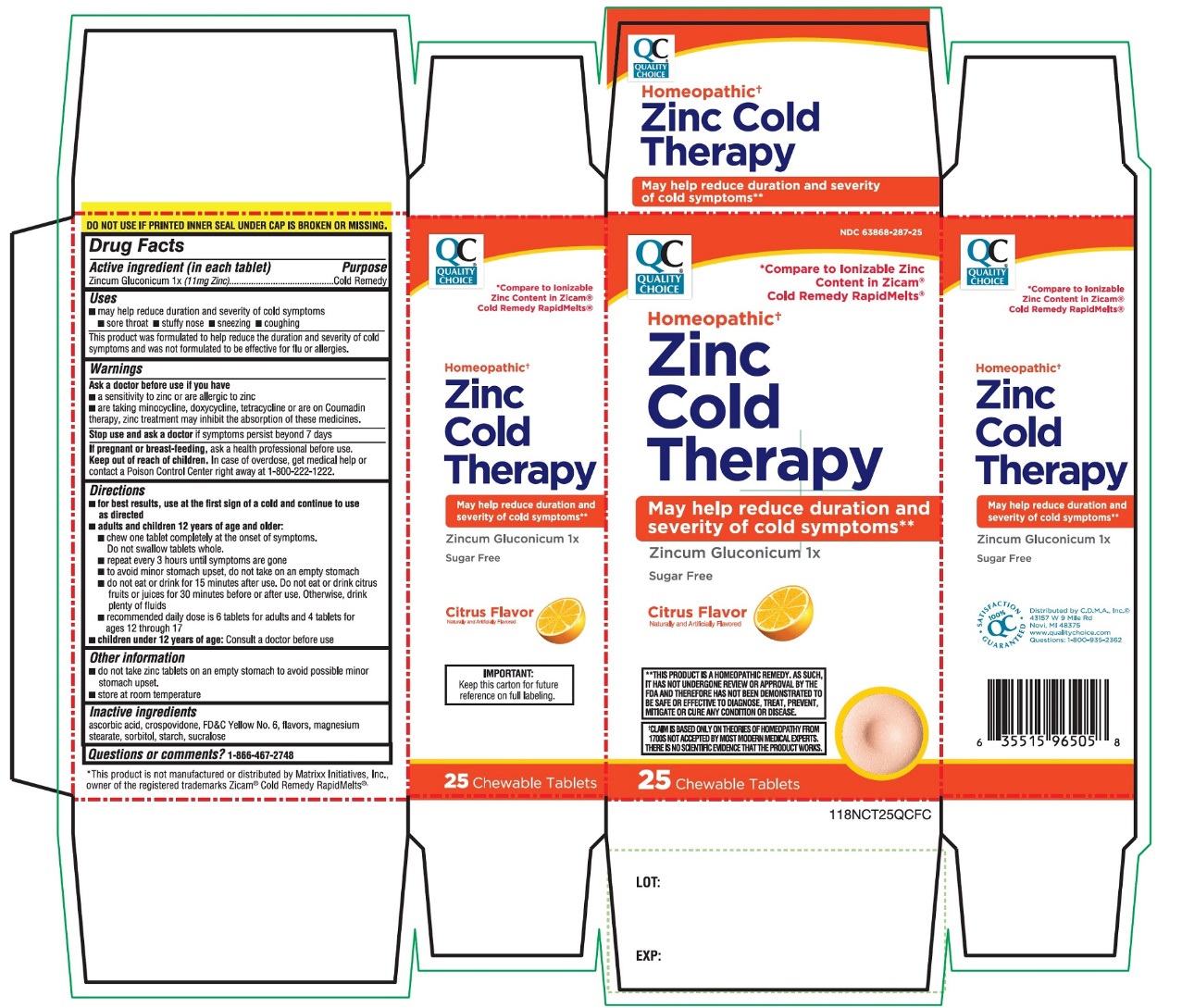 DRUG LABEL: Zinc Cold Therapy
NDC: 63868-287 | Form: TABLET
Manufacturer: Chain Drug Manufacturing Assn
Category: homeopathic | Type: HUMAN OTC DRUG LABEL
Date: 20251203

ACTIVE INGREDIENTS: ZINC GLUCONATE 1 [hp_X]/1 1
INACTIVE INGREDIENTS: ASCORBIC ACID; CROSPOVIDONE (120 .MU.M); FD&C YELLOW NO. 6; MAGNESIUM STEARATE; SORBITOL; STARCH, CORN; SUCRALOSE

QC Quality Choice Zinc Cold Therapy Citrus Flavor 25 Chewable Tablets

Drug Facts

ACTIVE INGREDIENT

Active ingredient (in each tablet)

Purpose

Cold Remedy

Zincum Gluconicum 1x(11 mg Zinc)

Uses

- may help reduce duration and severity of cold symptoms
  - sore throat
  - stuffy nose
  - sneezing
  - coughing
- This product was formulated to help reduce the duration and severity of cold symptoms and was not formulated to be effective for flu or allergies.

Warnings

ASK DOCTOR

Ask a doctor before use if you have

ASK DOCTOR

- a sensitivity to zinc or are allergic to zinc
- are taking minocycline, doxycycline, tetracycline or are on Coumadin therapy, zinc treatment may inhibit the absorption of these medicines.

Stop use and ask a doctorif symptoms persist beyond 7 days.

PREGNANCY OR BREAST FEEDING

If pregnant or breast-feeding,ask a health professional before use.

Keep out of reach of children.In case of overdose, get medical help or contact a Poison Control Center Right away at 1-800-222-1222

Directions

- For best results, use at the first sign of a cold and continue to use as directed
-
  1. adults and children 12 years of age and older:
    - chew one tablet at the onset of symptoms
    - repeat every 3 hours until symptoms are gone
    - to avoid minor stomach upset, do not take on an empty stomach.
    - do not eat or drink for 15 minutes after use. Do not eat or drink citrus fruits or juices for 30 minutes before or after use. Otherwise, drink plenty of fluids
    - recommended daily dose is 6 tablets for adults and 4 tablets for ages 12 through 17
  2. Children under 12 years of age:Consult a doctor before use.

Other information

- do not take zinc tablets on an empty stomach to avoid possible minor stomach upset.
- Store at room temperature

Inactive ingredients

ascorbic acid, crospovidone, FD&C yellow # 6, flavor. magnesium stearate, sorbitol, starch, sucralose

Questions or comments?

1-866-467-2748

PRINCIPAL DISPLAY PANEL

* Compare to ionizable Zinc Content in Zicam®Cold Remedy RapidMelts®

Homeopathic †

Zinc Cold Therapy

May help reduce duration and severity of cold symptoms**

Zincum Gluconicum 1x

Sugar Free

Citrus
Flavor

Naturally and Artificially Flavored

25CHEWABLE TABLETS

DO NOT USE IF PRINTED INNER SEAL UNDER CAP IS BROKEN OR MISSING

†CLAIM IS BASED ONLY ON THEORIES OF HOMEOPATHY FROM 1700S NOT ACCEPTED BY MOST MODERN MEDICAL EXPERTS .THERE IS NO SCIENTIFIC EVIDENCE THAT THE PRODUCT WORKS

**THIS PRODUCT IS A HOMEOPATHIC REMEDY, AS SUCH, IT HAS NOT UNDERGONE REVIEW ON APPROVAL BY THE FDA AND THEREFORE HAS NOT BEEN DEMONSTRATED TO BE SAFE OR EFFECTIVE TO DIAGNOSE, TREAT, PREVENT, MITIGATE OR CURE ANY CONDITION OR DISEASE.

IMPORTANT:Keep this carton for future reference on full labeling.

*This product is not manufactured or distributed by Matrixx Initiatives, Inc, owner of the registered trademarks Zicam®Cold Remedy Rapidmelts®

Distributed by C.D.M.A., Inc©

43157 W 9 Mile Rd

Novi, MI 48375-0995

www.qualitychoice.com

Questions: 248-449-9300